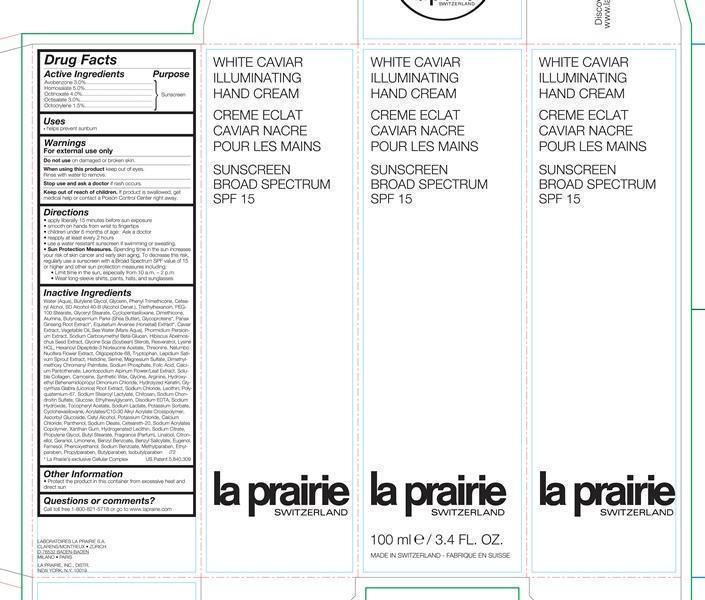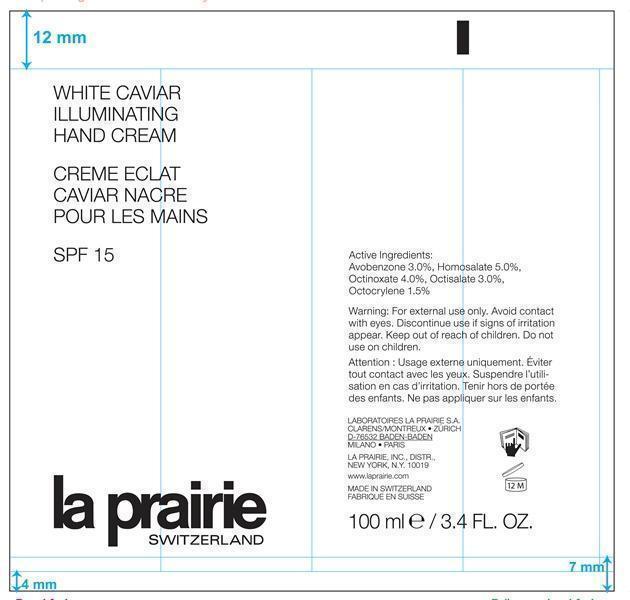 DRUG LABEL: White Caviar Illuminating Hand Sunscreen Broad Spectrum SPF 15
NDC: 68807-315 | Form: CREAM
Manufacturer: Temmentec AG
Category: otc | Type: HUMAN OTC DRUG LABEL
Date: 20170103

ACTIVE INGREDIENTS: AVOBENZONE 3 g/100 kg; HOMOSALATE 5 g/100 kg; OCTINOXATE 4 g/100 kg; OCTISALATE 3 g/100 kg; OCTOCRYLENE 1.5 g/100 kg
INACTIVE INGREDIENTS: WATER; BUTYLENE GLYCOL; GLYCERIN; PHENYL TRIMETHICONE; CETOSTEARYL ALCOHOL; TRIETHYLHEXANOIN; PEG-100 STEARATE; GLYCERYL MONOSTEARATE; CYCLOMETHICONE 5; DIMETHICONE; ALUMINUM OXIDE; SHEA BUTTER; ASIAN GINSENG; EQUISETUM ARVENSE TOP; CAVIAR, UNSPECIFIED; SODIUM CHLORIDE; PHORMIDIUM PERSICINUM; ABELMOSCHUS MOSCHATUS SEED; RESVERATROL; LYSINE HYDROCHLORIDE; THREONINE; NELUMBO NUCIFERA FLOWER; TRYPTOPHAN; GARDEN CRESS SPROUT; HISTIDINE; SERINE; MAGNESIUM SULFATE; SODIUM PHOSPHATE; FOLIC ACID; CALCIUM PANTOTHENATE; LEONTOPODIUM ALPINUM FLOWERING TOP; CARNOSINE; SYNTHETIC WAX (1200 MW); GLYCINE; ARGININE; HYDROXYETHYL BEHENAMIDOPROPYL DIMONIUM CHLORIDE; LICORICE; LECITHIN, SOYBEAN; SODIUM STEAROYL LACTYLATE; SODIUM CHONDROITIN SULFATE (PORCINE; 5500 MW); ETHYLHEXYLGLYCERIN; EDETATE DISODIUM; SODIUM HYDROXIDE; .ALPHA.-TOCOPHEROL ACETATE; SODIUM LACTATE; POTASSIUM SORBATE; CYCLOMETHICONE 6; CARBOMER COPOLYMER TYPE A (ALLYL PENTAERYTHRITOL CROSSLINKED); ASCORBYL GLUCOSIDE; CETYL ALCOHOL; POTASSIUM CHLORIDE; CALCIUM CHLORIDE; PANTHENOL; SODIUM OLEATE; XANTHAN GUM; HYDROGENATED SOYBEAN LECITHIN; SODIUM CITRATE; PROPYLENE GLYCOL; BUTYL STEARATE; LINALOOL, (+)-; .BETA.-CITRONELLOL, (R)-; GERANIOL; LIMONENE, (+)-; BENZYL BENZOATE; BENZYL SALICYLATE; EUGENOL; FARNESOL; PHENOXYETHANOL; SODIUM BENZOATE; METHYLPARABEN; ETHYLPARABEN; PROPYLPARABEN; BUTYLPARABEN; ISOBUTYLPARABEN

White Caviar Illuminating Hand SPF 15

Active Ingredients Purpose

Avobenzone 3.0% Sunscreen

Homosalate 5.0% Sunscreen

Octinoxate 4.0% Sunscreen

Octisalate 3.0% Sunscreen

Octocrylene 1.5% Sunscreen

Uses
helps prevent sunburn

Keep out of reach of children. If swallowed, get medical help or contact a poison control center right away.

Stop use and ask a doctor if rash occurs

Warnings

For external use only
Do not use on damaged or broken skin
When using this product keep out of eyes. Rinse with water to remove

Directions
Apply liberally 15 minutes before sun exposure

Smooth on hands front wrists to fingertips

Children under 6 months: Ask a doctor

Reapply at least every 2 hours
Use a water resistant sunscreen if swimming or sweating

Sun Protection Measures. Spending time in the sun increases your risk of skin
cancer and early skin aging. To decrease this risk, regularly use a sunscreen
with broad spectrum SPF of 15 or higher and other sun protection measures
including:
limit time in the sun, especially from 10 a.m. - 2 p.m.
wear long-sleeve shirts, pants, hats, and sunglasses

INACTIVE INGREDIENT

Water (Aqua), Butylene Glycol, Glycerin, Phenyl Trimethicone, Cetearyl Alcohol, SD Alcohol 40-B (Alcohol Denat), Triethylhexanoin, PEG-100 Stearate, Glyceryl Stearate, Cyclopentasiloxane, Dimethicone, Alumina, Butyrospermum Parkii (Shea Butter), Glycoproteins, Panax Ginseng Root Extract, Equisetum Arvense (Horsetail) Extract, Caviar Extract, Vegetable Oil, Sea Water (Maris Aqua), Phormidium Persicinium Extract, Sodium Carboxymethyl Beta-Glucan, Hibiscus Abelmoschus Seed Extract, Glycine Soja (Soybean) Sterols, Resveratrol, Lysine HCL, Hexanoyl Dipeptide-3 Norleucine Acetate, Threonine, Nelumbo Nucifera Flower Extract, Oligopeptide-68, Tryptophan, Lepidium Sativumm Sprout Extract, Histidine, Serine, Magnesium Sulfate, Dimethylmethoxy Chromanyl Palmitate, Sodium Phosphate, Folic Acid, Calcium Pantothenate, Leontopodium Alpinium Flower/Leaf Extract, Soluble Collagen, Carnosine, Synthetic Wax, Glycine, Arginine, Hydroxyethyl Behenamidopropyl Dimonium Chloride, Hydrolyzed Keratin, Glycyrrhiza Glabra (Licorice) Root Extract, Sodium Chloride, Lecithin, Polyquaternium-67, Sodium Stearoyl Lactylate, Chitosan, Sodium Chondroitin Sulfate, Glucose, Ethylhexylglycerin, Disodium EDTA, Sodium Hydroxide, Tocopheryl Acetate, Sodium Lactate, Potassium Sorbate, Cyclohexasiloxane, Acrylates/C10-30 Alkyl Acrylate Crosspolymer, Ascorbyl Glucoside, Cetyl Alcohol, Potassium Chloride, Calcium Chloride, Panthenol, Sodium Oleate, Ceteareth-20, Sodium Acrylates Copolymer, Xanthan Gum, Hydrogenated Lecithin, Sodium Citrate, Propylene Glycol, Butyl Stearate, Fragrance/Parfum, Linalool, citronellol, Geraniol, Limonene, Benzyl Benzoate, Benzyl Slicylate, Eugenol, Farnesol, Phenoxyethanol, Sodium Benzoate, Methylparaben, Ethylparaben, Propylparaben, Butylparaben, Isobutylparaben.

PACKAGE LABEL

White Caviar Illuminating Hand Cream

Creme Eclat Caviar Nacre Pour les mains

Sunscreen Broad Spectrum SPF 15

La Prairie Switzerland

100 ml/ 3.4 Fl Oz.